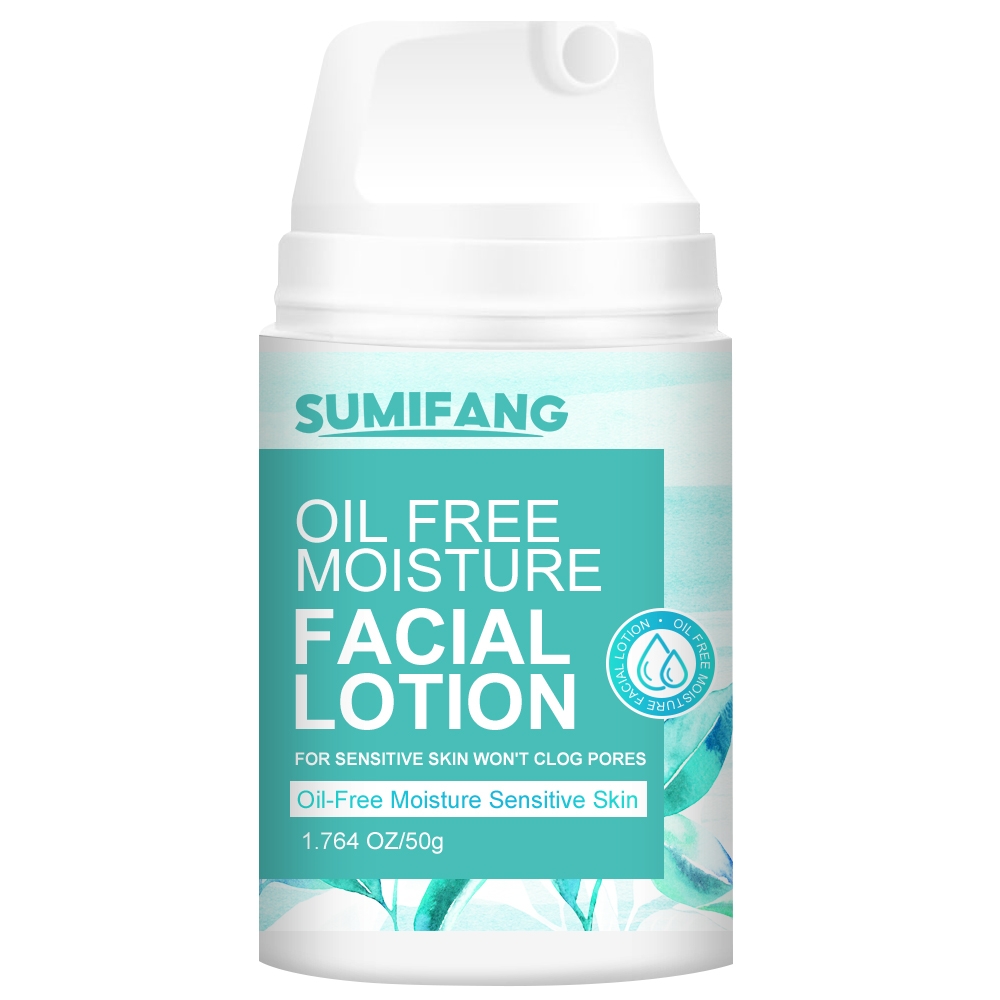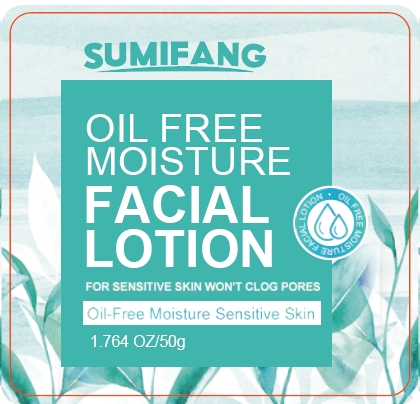 DRUG LABEL: FACIALLOTION
NDC: 84025-145 | Form: LOTION
Manufacturer: Guangzhou Yanxi Biotechnology Co.. Ltd
Category: otc | Type: HUMAN OTC DRUG LABEL
Date: 20240814

ACTIVE INGREDIENTS: GLYCERIN 3 mg/50 g; HYALURONIC ACID 5 mg/50 g
INACTIVE INGREDIENTS: WATER

DOSAGE AND ADMINISTRATION

Cream for moisturizing and firming facial skin

WARNINGS

keep out of children

INACTIVE INGREDIENT

Aqua

INDICATIONS AND USAGE

For daily skin care

Keep out of children

PURPOSE

Effectively moisturizes facial skin and repairs skin pores